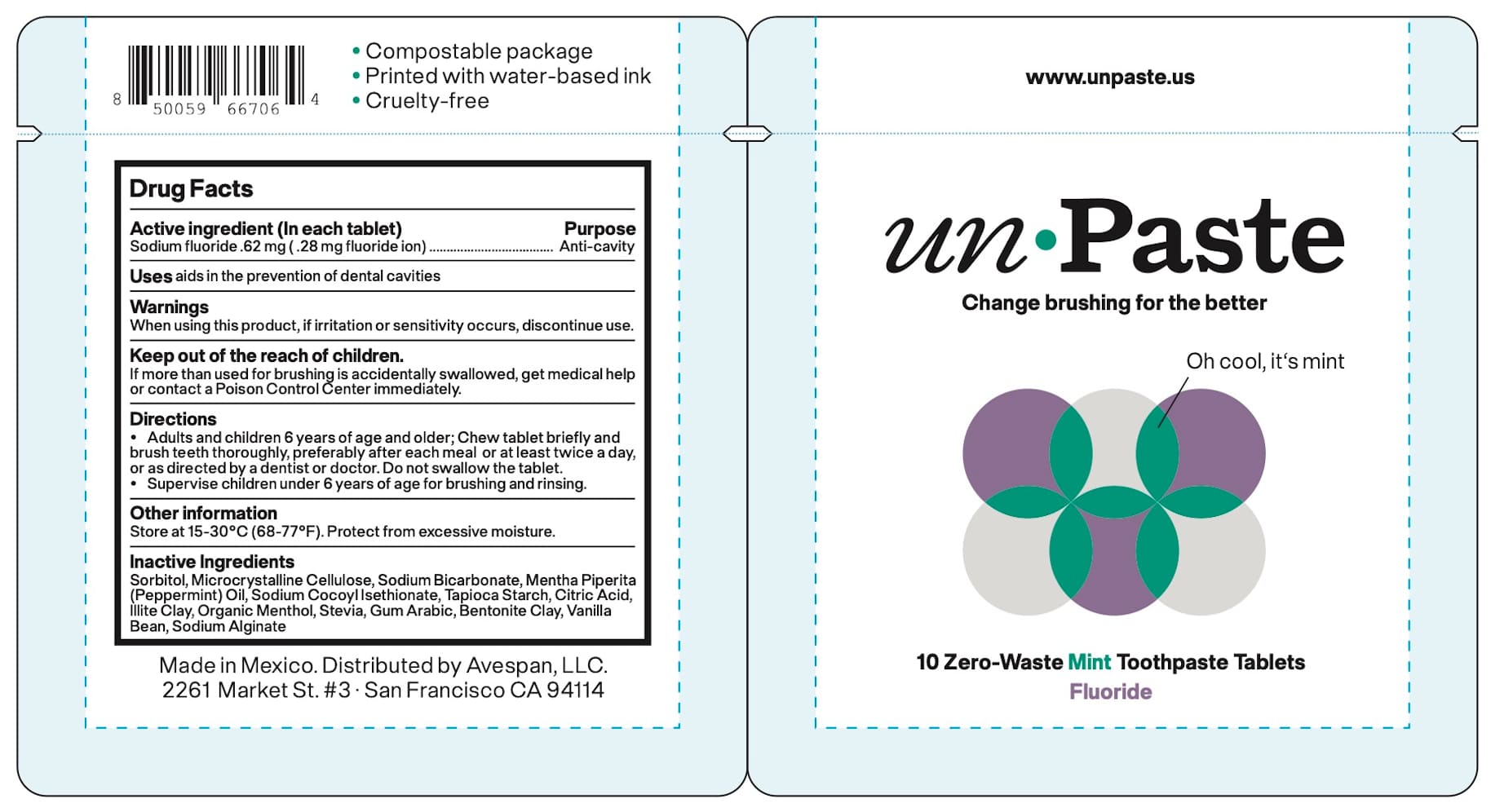 DRUG LABEL: Unpaste
NDC: 74355-666 | Form: TABLET, CHEWABLE
Manufacturer: Avespan LLC
Category: otc | Type: HUMAN OTC DRUG LABEL
Date: 20250325

ACTIVE INGREDIENTS: SODIUM FLUORIDE 0.62 mg/1 1
INACTIVE INGREDIENTS: SODIUM COCOYL ISETHIONATE; CELLULOSE, MICROCRYSTALLINE; SODIUM BICARBONATE; PEPPERMINT; ILLITE; BENTONITE; SODIUM ALGINATE; CITRIC ACID; MENTHOL; STARCH, TAPIOCA; VANILLA; ACACIA; SORBITOL; STEVIOL

Avespan-Muyme Mint 2025

Active Ingredient(s)

Sodium Fluoride 0.62mg (28 mg flouride ion)

Purpose

Anti-cavity

Use

aids in the prevention of dental cavities

Warnings

- When using this product, if irritation or sensitivity occurs discontinue use.
- Keep out of the reach of children. If more than used for brushing is accidentally swallowed, get medical help or contact a Poison Control Center immediately.

When using this product, if irritation or sensitivity occurs discontinue use.

KEEP OUT OF REACH OF CHILDREN

If more than used for brushing is accidentally swallowed, get medical help or contact a Poison Control Center immediately.

Directions

- Adults and children 6 years of age and older; chew one tablet briefly and brush teeth thoroughly, preferably after each meal or at least twice a day, or as directed by a dentist or doctor.
- Do not swallow the tablet.
- Supervise children under 6 years of age for brushing and rinsing.

Other information

Store at 25-30°C (68-77°F). Protect from excessive moisture.

Inactive ingredients

Sorbitol, Microcrystalline Cellulose, Sodium Bicarbonate, Mentha Piperita
(Peppermint) Oil, Sodium CocoylIsethionate, Tapioca Starch, Citric Acid,
Illite Clay, Organic Menthol, Stevia, Gum Arabic, Bentonite Clay, Vanilla
Bean, Sodium Alginate

Package Label - Principal Display Panel

Mint 10 Tablets; NDC: 74355-666-11